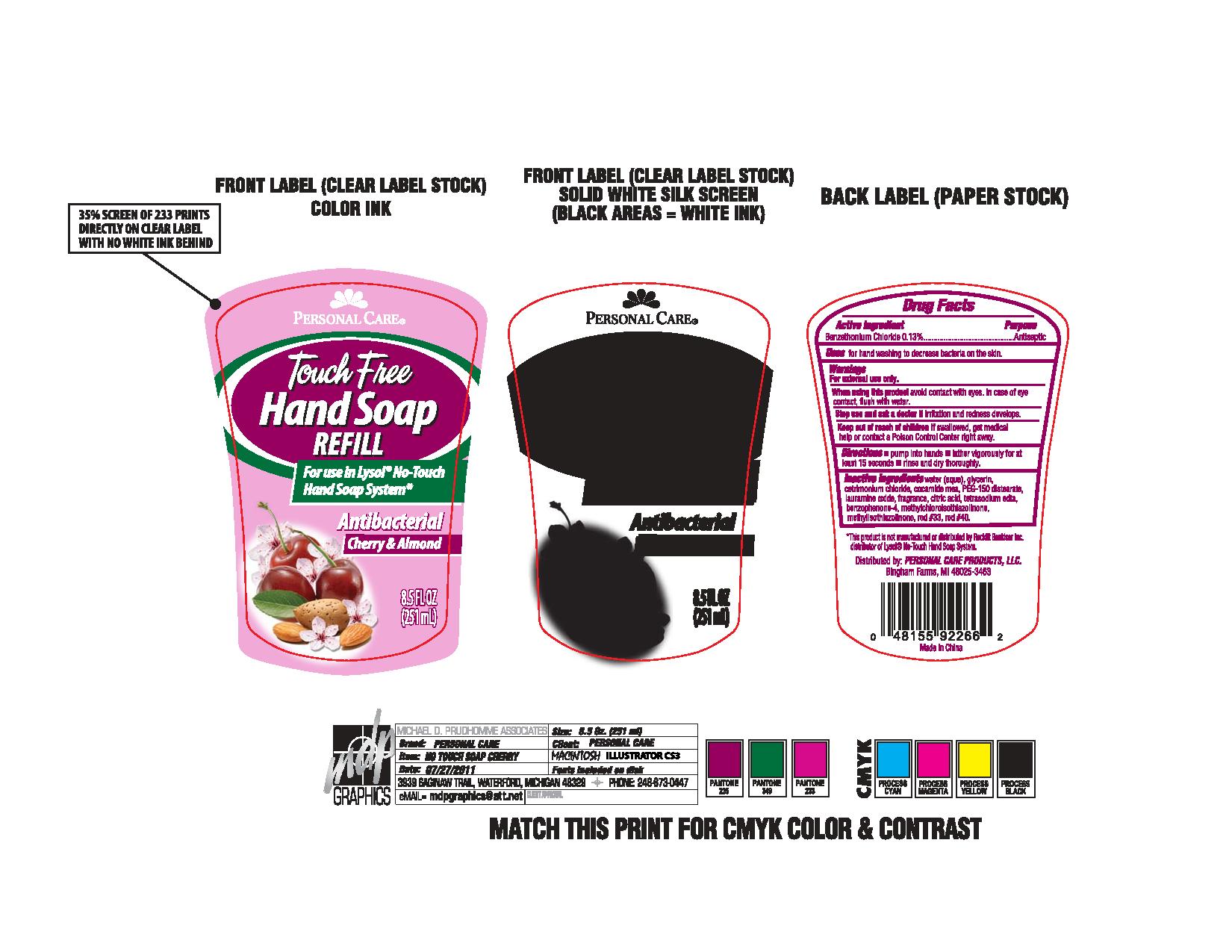 DRUG LABEL: Touch Free Hand
NDC: 29500-9710 | Form: SOAP
Manufacturer: Personal Care Products
Category: otc | Type: HUMAN OTC DRUG LABEL
Date: 20110728

ACTIVE INGREDIENTS: BENZETHONIUM CHLORIDE .33 mL/251 mL
INACTIVE INGREDIENTS: WATER; GLYCERIN; CETRIMONIUM CHLORIDE; COCO MONOETHANOLAMIDE; PEG-150 DISTEARATE; LAURAMINE OXIDE; CITRIC ACID; EDETATE SODIUM; METHYLCHLOROISOTHIAZOLINONE; METHYLISOTHIAZOLINONE; D&C RED NO. 33

Touch Free Hand

ACTIVE INGREDIENT

Enter section text here

Purpose antiseptic

Keep out of reach of children. If swallowed, get medical help or contact a Poison Control Center right away.

INDICATIONS AND USAGE

Uses for hand washing to decrease bacteria on the skin.

Warnings
For external use only
When using this product avoid contact with eyes.In case of eye contact, flush with water.
Stop use and ask a doctor if irritation and redness develops.

Directions

Pump into hands

lather vigorously for at least 15 seconds

rinse and dry thoroughly.

Inactive ingredients

Water (aqua), glycerin, cetrimonium chloride, cocamide mea, PEG-150 distearate, lauramine oxide, fragrance, citric acid, tetrasodium edta, benzophenone-4, methylchloroisothiazolinone, methylisothiazolinone, red #33, red #40.

PACKAGE LABEL

Personal Care

Touch Free Hand Soap Refill

For use in lysol No touch Hand Soap System

Antibacterial

Cherry and Almond

8.5 Fl Oz (251 ml)